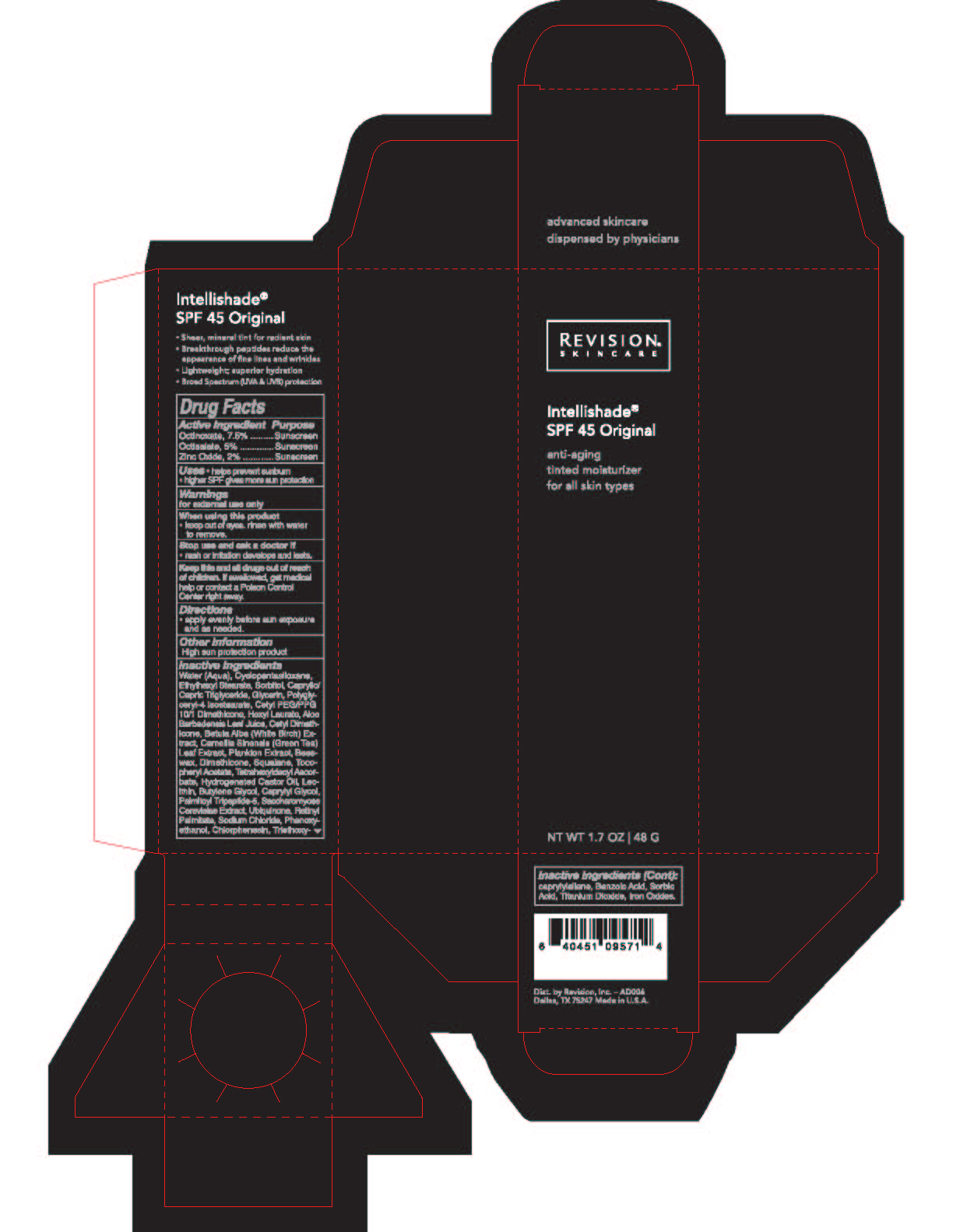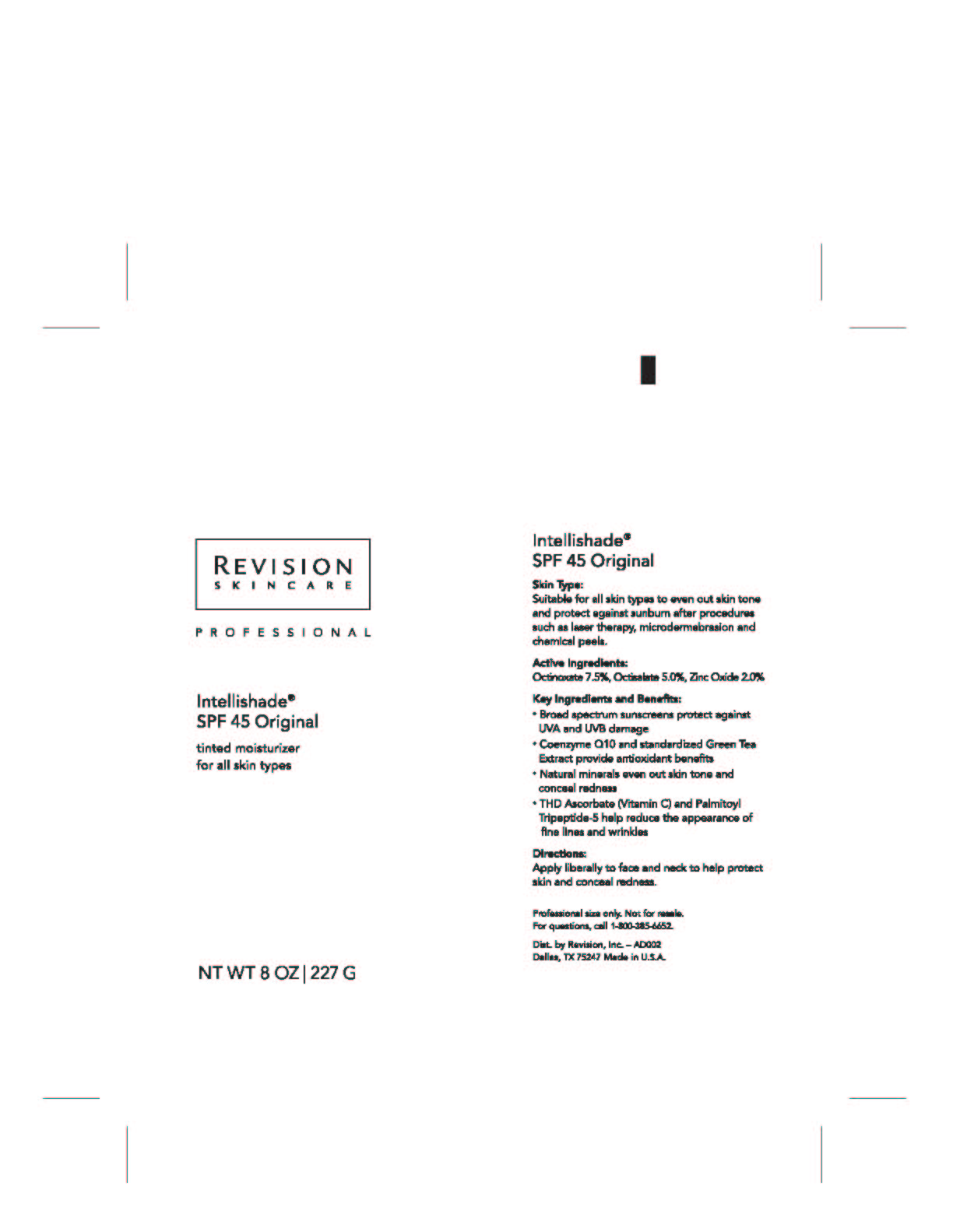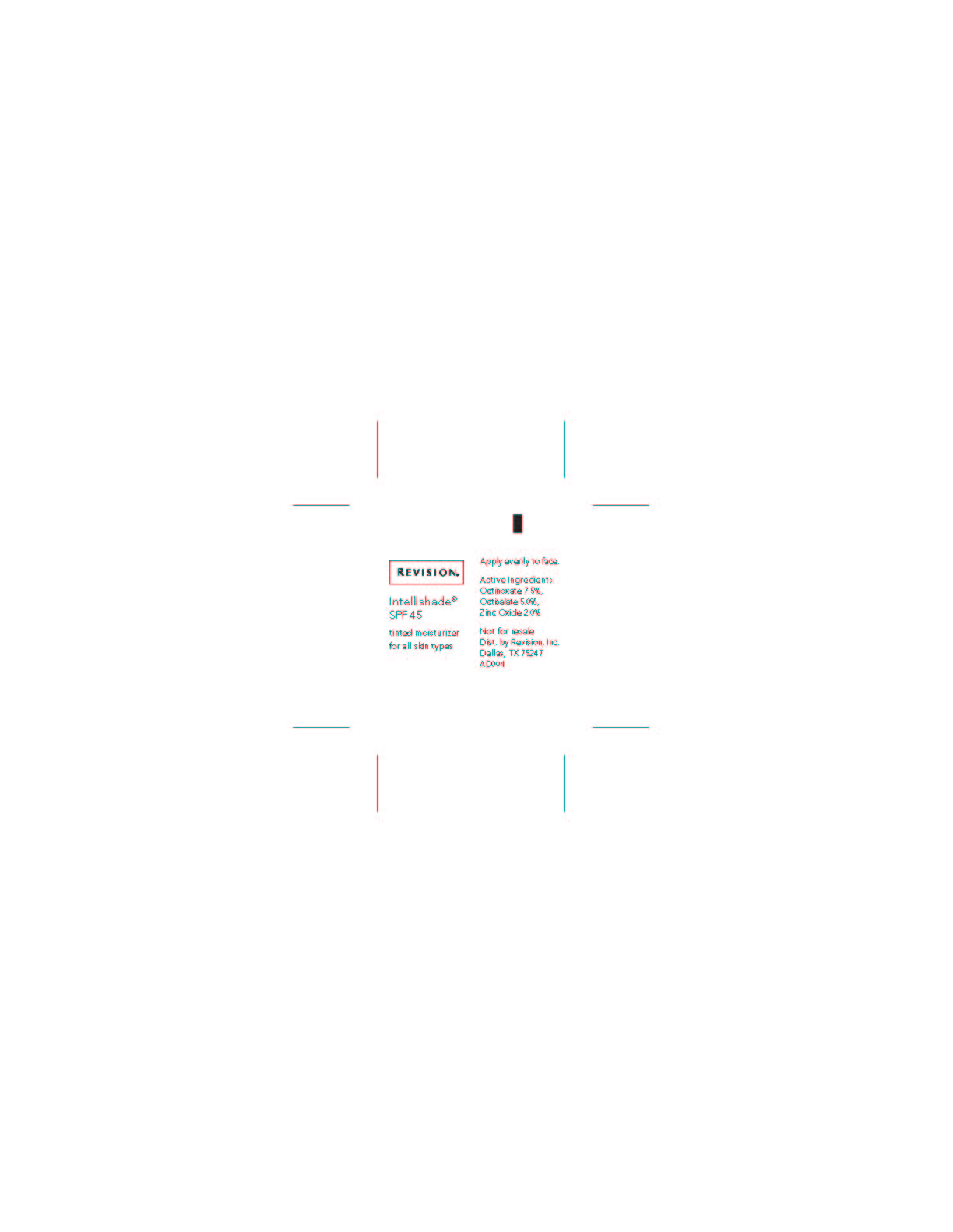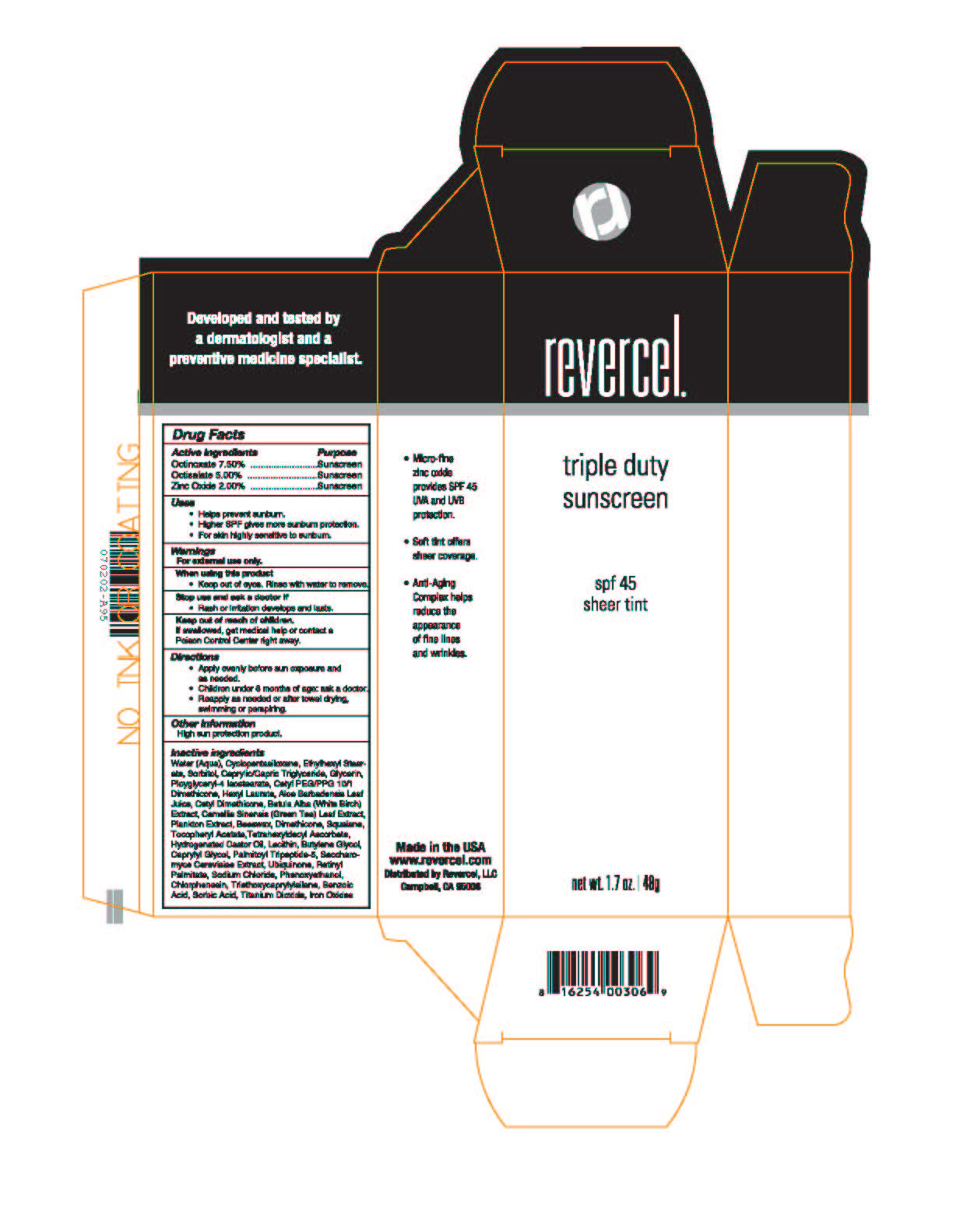 DRUG LABEL: Tinted SPF 45
NDC: 10477-2627 | Form: CREAM
Manufacturer: Goodier Cosmetics, LP
Category: otc | Type: HUMAN OTC DRUG LABEL
Date: 20111205

ACTIVE INGREDIENTS: OCTINOXATE 7.5 g/100 g; OCTISALATE 5 g/100 g; ZINC OXIDE 2 g/100 g
INACTIVE INGREDIENTS: WATER; CYCLOMETHICONE 5; ETHYLHEXYL STEARATE; SORBITOL; MEDIUM-CHAIN TRIGLYCERIDES; GLYCERIN; POLYGLYCERYL-4 ISOSTEARATE; CETYL PEG/PPG-10/1 DIMETHICONE (HLB 1.5); HEXYL LAURATE; ALOE VERA LEAF; BETULA PUBESCENS BARK; GREEN TEA LEAF; WHITE WAX; DIMETHICONE; SQUALANE; .ALPHA.-TOCOPHEROL ACETATE, D-; TETRAHEXYLDECYL ASCORBATE; HYDROGENATED CASTOR OIL; LECITHIN, SOYBEAN; BUTYLENE GLYCOL; CAPRYLYL GLYCOL; PALMITOYL TRIPEPTIDE-5; UBIDECARENONE; VITAMIN A PALMITATE; PHENOXYETHANOL; CHLORPHENESIN; TRIETHOXYCAPRYLYLSILANE; BENZOIC ACID; SORBIC ACID; FERRIC OXIDE RED; FERRIC OXIDE YELLOW; FERROSOFERRIC OXIDE; TITANIUM DIOXIDE

Revision Skincare 1.7oz Retail Intellishade®

Intellishade®
SPF 45 Original

anti-aging
tinted moisturizer
for all skin types

NT WT 1.7 OZ / 48 G

Active Ingredient Purpose

Octinoxate 7.5% Sunscreen
Octisalate 5% Sunscreen
Zinc Oxide 2% Sunscreen

Uses

- helps prevent sunburn
- higher SPF gives more sun protection
- for skin highly sensitive to sunburn

Warnings

for external use only

When using this product

- keep out of eyes, rinse with water to remove.

Stop use and ask a doctor if

- rash or irritation develops and lasts.

Keep this and all drugs out of reach
of children. If swallowed, get medical
help or contact a Poison Control
Center right away.

Directions

- apply evenly before sun exposure and as needed.

Other Information
High sun protection product

Inactive ingredients
Water (Aqua), Cyclopentasiloxane, Ethylhexyl Stearate, Sorbitol,
Caprylic/Capric Triglyceride, Glycerin, Polyglyceryl-4 Isostearate,
Cetyl PEG/PPG 10/1 Dimethicone, Hexyl Laurate, Aloe Barbadensis
Leaf Juice, Cetyl Dimethicone, Betula Alba (White Birch) Extract,
Camellia Sinensis (Green Tea) Leaf Extract, Plankton Extract,
Beeswax, Dimethicone, Squalane, Tocopheryl Acetate, Tetrahexyldecyl
Ascorbate, Hydrogenated Castor Oil, Lecithin, Butylene Glycol, Caprylyl
Glycol, Palmitoyl Tripeptide-5, Saccharomyces Cerevisiae Extract,
Ubiquinone, Retinyl Palmitate, Sodium Chloride, Phenoxyethanol,
Chlorphenesin, Triethoxycaprylylsilane, Benzoic Acid, Sorbic Acid,
Titanium Dioxide, Iron Oxides

Dist. by Revision, Inc.
Dallas, TX 75247 Made in U.S.A.

Revercel 1.7oz Retail Triple Duty Sunscreen

triple duty
sunscreen
spf 45
sheer tint
net. wt. 1.7oz / 48g

Active Ingredient Purpose

Octinoxate 7.50% Sunscreen
Octisalate 5.00% Sunscreen
Zinc Oxide 2.00% Sunscreen

Uses

- Helps prevent sunburn.
- Higher SPF gives more sun protection.
- For skin highly sensitive to sunburn.

Warnings

For external use only.

When using this product

- Keep out of eyes. Rinse with water to remove.

Stop use and ask a doctor if

- Rash or irritation develops and lasts.

Keep out of reach of children.
If swallowed, get medical help or contact a
Poison Control Center right away.

Directions

- Apply evenly before sun exposure and as needed.
- Children under 6 months of age: ask a doctor.
- Reapply as needed or after towel drying, swimming or perspiring.

Other Information
High sun protection product.

Inactive ingredients
Water (Aqua), Cyclopentasiloxane, Ethylhexyl Stearate, Sorbitol,
Caprylic/Capric Triglyceride, Glycerin, Polyglyceryl-4 Isostearate,
Cetyl PEG/PPG 10/1 Dimethicone, Hexyl Laurate, Aloe Barbadensis
Leaf Juice, Cetyl Dimethicone, Betula Alba (White Birch) Extract,
Camellia Sinensis (Green Tea) Leaf Extract, Plankton Extract,
Beeswax, Dimethicone, Squalane, Tocopheryl Acetate, Tetrahexyldecyl
Ascorbate, Hydrogenated Castor Oil, Lecithin, Butylene Glycol, Caprylyl
Glycol, Palmitoyl Tripeptide-5, Saccharomyces Cerevisiae Extract,
Ubiquinone, Retinyl Palmitate, Sodium Chloride, Phenoxyethanol,
Chlorphenesin, Triethoxycaprylylsilane, Benzoic Acid, Sorbic Acid,
Titanium Dioxide, Iron Oxides

Made in the USA

Distributed by Revercel, LLC
Cambell, CA 95008

Revision Skincare 8oz Professional Intellishade®

Intellishade®
SPF 45 Original
tinted moisturizer
for all skin types
NT WT 8 OZ / 227 G

Skin Type:

Suitable for all skin types to even out skin tone
and protect against sunburn after procedures
such as laser therapy, microdermabrasion and
chemical peels.

Active Ingredients:

Octinoxate 7.5%, Octisalate 5.0%, Zinc Oxide 2.0%

Key Ingredients and Benefits:

- Broad spectrum sunscreens protect against UVA and UVB damage
- Coenzyme Q10 and standardized Green Tea Extract provide antioxidant benefits
- Natural minerals even out skin tone and conceal redness
- THD Ascorbate (Vitamin C) and Palmitoyl Tripeptide-5 help reduce the appearance of fine lines and wrinkles

Directions:

Apply liberally to face and neck to help protect skin and conceal redness.

Professional size only. Not for resale.

Dist. by Revision, Inc
Dallas, TX 75247 Made in U.S.A.